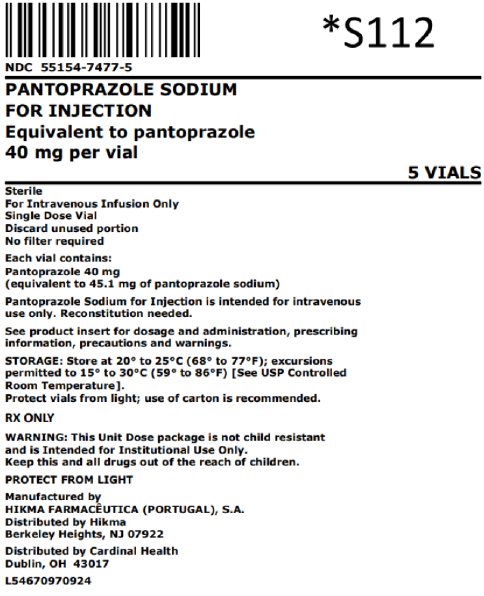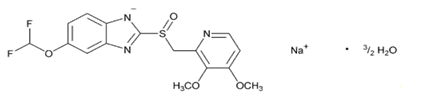 DRUG LABEL: Pantoprazole Sodium
NDC: 55154-7477 | Form: INJECTION, POWDER, LYOPHILIZED, FOR SOLUTION
Manufacturer: Cardinal Health 107, LLC
Category: prescription | Type: HUMAN PRESCRIPTION DRUG LABEL
Date: 20251013

ACTIVE INGREDIENTS: PANTOPRAZOLE SODIUM 40 mg/1 1
INACTIVE INGREDIENTS: SODIUM HYDROXIDE

HIGHLIGHTS OF PRESCRIBING INFORMATION

These highlights do not include all the information needed to use PANTOPRAZOLE SODIUM FOR INJECTION safely and effectively. See full prescribing information for PANTOPRAZOLE SODIUM FOR INJECTION.
PANTOPRAZOLE SODIUM for injection, for intravenous use
Initial U.S. Approval: 2000

1 INDICATIONS AND USAGE

Pantoprazole Sodium for Injection is a proton pump inhibitor (PPI) indicated in adults for the following:

• Short-term treatment (7 to 10 days) of gastroesophageal reflux disease (GERD) associated with a history of erosive esophagitis (EE). (1.1)

• Pathological hypersecretion conditions, including Zollinger-Ellison (ZE) syndrome. (1.2)

2 DOSAGE AND ADMINISTRATION

GERD Associated with EE (2.1):

• The recommended adult dosage is 40 mg administered once daily by intravenous infusion for 7 to 10 days.

Pathological Hypersecretory Conditions, Including ZE Syndrome (2.3):

• The recommended adult dosage is 80 mg administered every 12 hours by intravenous infusion. See the full prescribing information for information on how to adjust dosing for individual patient needs.

Administration (2.2, 2.4):

• Only for intravenous infusion.

• The intravenous infusion can be administered over 2 minutes or 15 minutes.

• For information on how to prepare and administer for each indication, see the full prescribing information.

3 DOSAGE FORMS AND STRENGTHS

For Injection: 40 mg pantoprazole lyophilized powder in a single-dose vial for reconstitution (3)

4 CONTRAINDICATIONS

• Patients with known hypersensitivity to any component of the formulation or to substituted benzimidazoles. (4)

• Patients receiving rilpivirine-containing products (4, 7)

5 WARNINGS AND PRECAUTIONS

• Gastric Malignancy: In adults, symptomatic response to therapy with Pantoprazole Sodium for Injection does not preclude the presence of gastric malignancy. Consider additional follow-up and diagnostic testing. (5.1)

• Injection Site Reactions: Thrombophlebitis is associated with intravenous use. (5.2)

• Acute Tubulointerstitial Nephritis: Discontinue treatment and evaluate patients. (5.3)

• Clostridium difficile-Associated Diarrhea: PPI therapy may be associated with increased risk. (5.4)

• Bone Fracture: Long-term and multiple daily dose PPI therapy may be associated with an increased risk for osteoporosis-related fractures of the hip, wrist or spine. (5.5)

• Severe Cutaneous Adverse Reactions: Discontinue at the first signs or symptoms of severe cutaneous adverse reactions or other signs of hypersensitivity and consider further evaluation. (5.6)

• Cutaneous and Systemic Lupus Erythematosus: Mostly cutaneous; new onset or exacerbation of existing disease; discontinue Pantoprazole Sodium for Injection and refer to specialist for evaluation. (5.7)

• Hepatic Effects: Elevations of transaminases observed. (5.8)

• Hypomagnesemia and Mineral Metabolism: Reported rarely with prolonged treatment with PPIs. (5.9)

• Fundic Gland Polyps: Risk increases with long-term use, especially beyond one year. Use the shortest duration of therapy. (5.10)

6 ADVERSE REACTIONS

Most common adverse reactions (>2%) are: headache, diarrhea, nausea, abdominal pain, vomiting, flatulence, dizziness, and arthralgia. (6.1)

To report SUSPECTED ADVERSE REACTIONS, contact Hikma Pharmaceuticals USA Inc. at 1-877-845-0689 or FDA at 1-800-FDA-1088 or www.fda.gov/medwatch.

7 DRUG INTERACTIONS

See full prescribing information for a list of clinically important drug interactions. (7)

8 USE IN SPECIFIC POPULATIONS

Pregnancy: Based on animal data, may cause fetal harm. (8.1)

FULL PRESCRIBING INFORMATION

1 INDICATIONS AND USAGE

1.1 Gastroesophageal Reflux Disease Associated with a History of Erosive Esophagitis

Pantoprazole Sodium for Injection is indicated for short-term treatment (7 to 10 days) of adult patients with gastroesophageal reflux disease (GERD) and a history of erosive esophagitis (EE).

Safety and efficacy of Pantoprazole Sodium for Injection as a treatment of patients with GERD and a history of EE for more than 10 days have not been demonstrated.

1.2 Pathological Hypersecretion Including Zollinger-Ellison Syndrome

Pantoprazole Sodium for Injection is indicated for the treatment of pathological hypersecretory conditions including Zollinger-Ellison (ZE) Syndrome in adults.

2 DOSAGE AND ADMINISTRATION

2.1 Dosage for Gastroesophageal Reflux Disease Associated With a History of Erosive Esophagitis

The recommended adult dosage of Pantoprazole Sodium for Injection is 40 mg given once daily by intravenous infusion for 7 to 10 days.

Discontinue treatment with Pantoprazole Sodium for Injection as soon as the patient is able to receive treatment with pantoprazole sodium delayed-release tablets or oral suspension.

Data on the safe and effective dosing for conditions other than those described [see Indications and Usage (1)] such as life-threatening upper gastrointestinal bleeds, are not available. Pantoprazole Sodium for Injection 40 mg once daily does not raise gastric pH to levels sufficient to contribute to the treatment of such life-threatening conditions.

2.2 Preparation and Administration Instructions for Gastroesophageal Reflux Disease Associated with a History of Erosive Esophagitis

For intravenous infusion only.

Fifteen Minute Infusion

1. Reconstitute Pantoprazole Sodium for Injection with 10 mL of 0.9% Sodium Chloride Injection, USP

2. Further dilute with 100 mL of 5% Dextrose Injection, USP, 0.9% Sodium Chloride Injection, USP, or Lactated Ringer's Injection, USP, to a final concentration of approximately 0.4 mg/mL.

3. Inspect the diluted Pantoprazole Sodium for Injection solution visually for particulate matter and discoloration prior to and during administration.

4. Administer intravenously over a period of approximately 15 minutes at a rate of approximately 7 mL/minute.

Storage

The reconstituted solution may be stored for up to 6 hours at room temperature prior to further dilution. The diluted solution may be stored at room temperature and must be used within 24 hours from the time of initial reconstitution. Both the reconstituted solution and the diluted solution do not need to be protected from light.

Do not freeze either the reconstituted or diluted solutions.

Two Minute Infusion

1. Reconstitute Pantoprazole Sodium for Injection with 10 mL of 0.9% Sodium Chloride Injection, USP, to a final concentration of approximately 4 mg/mL.

2. Inspect the diluted Pantoprazole Sodium for Injection solution visually for particulate matter and discoloration prior to and during administration.

3. Administer intravenously over a period of at least 2 minutes.

Storage

The reconstituted solution may be stored for up to 24 hours at room temperature prior to intravenous infusion and does not need to be protected from light.

Do not freeze either the reconstituted or diluted solutions.

2.3 Dosage for Pathological Hypersecretion Including Zollinger-Ellison Syndrome

The recommended adult dosage of Pantoprazole Sodium for Injection is 80 mg intravenously every 12 hours. The frequency of dosing can be adjusted to individual patient needs based on acid output measurements. In those patients who need a higher dosage, 80 mg intravenously every 8 hours is expected to maintain acid output below 10 mEq/h. Daily doses higher than 240 mg or administered for more than 6 days have not been studied [see Clinical Studies (14.2)]. Transition from oral to intravenous and from intravenous to oral formulations of gastric acid inhibitors should be performed in such a manner to ensure continuity of effect of suppression of acid secretion. Patients with ZE Syndrome may be vulnerable to serious clinical complications of increased acid production even after a short period of loss of effective inhibition.

2.4 Preparation and Administration Instructions for Pathological Hypersecretion Including Zollinger-Ellison Syndrome

For intravenous infusion only.

Fifteen Minute Infusion

1. Reconstitute each vial of Pantoprazole Sodium for Injection with 10 mL of 0.9% Sodium Chloride Injection, USP.

2. Combine the contents of the two vials and further dilute with 80 mL of 5% Dextrose Injection, USP, 0.9% Sodium Chloride Injection, USP, or Lactated Ringer's Injection, USP, to a total volume of 100 mL with a final concentration of approximately 0.8 mg/mL.

3. Inspect the diluted Pantoprazole Sodium for Injection solution visually for particulate matter and discoloration prior to and during administration.

4. Administer intravenously over a period of approximately 15 minutes at a rate of approximately 7 mL/minute.

Storage

The reconstituted solution may be stored for up to 6 hours at room temperature prior to further dilution. The diluted solution may be stored at room temperature and must be used within 24 hours from the time of initial reconstitution. Both the reconstituted solution and the diluted solution do not need to be protected from light.

Do not freeze either the reconstituted or diluted solutions.

Two Minute Infusion

1. Reconstitute Pantoprazole Sodium for Injection with 10 mL of 0.9% Sodium Chloride Injection, USP, per vial to a final concentration of approximately 4 mg/mL.

2. Inspect the reconstituted Pantoprazole Sodium for Injection solution visually for particulate matter and discoloration prior to and during administration.

3. Administer the total volume from both vials intravenously over a period of at least 2 minutes.

Storage

The reconstituted solution may be stored for up to 24 hours at room temperature prior to intravenous infusion and does not need to be protected from light.

Do not freeze the reconstituted solution.

2.5 Compatibility Information

• Administer Pantoprazole Sodium for Injection intravenously through a dedicated line or through a Y-site.

• Flush the intravenous line before and after administration of Pantoprazole Sodium for Injection with either 5% Dextrose Injection, USP, 0.9% Sodium Chloride Injection, USP, or Lactated Ringer's Injection, USP.

• When administered through a Y-site, Pantoprazole Sodium for Injection is compatible with the following solutions: 5% Dextrose Injection, USP, 0.9% Sodium Chloride Injection, USP, or Lactated Ringer's Injection, USP.

• Midazolam HCl has been shown to be incompatible with Y-site administration of Pantoprazole Sodium for Injection.

• Pantoprazole Sodium for Injection may not be compatible with products containing zinc.

• When administered through a Y-site, immediately discontinue the infusion if precipitation or discoloration occurs.

3 DOSAGE FORMS AND STRENGTHS

For Injection: 40 mg pantoprazole white to off-white lyophilized powder in a single-dose vial for reconstitution.

4 CONTRAINDICATIONS

• Pantoprazole Sodium for Injection is contraindicated in patients with known hypersensitivity reactions including anaphylaxis to the formulation or any substituted benzimidazole. Hypersensitivity reactions may include anaphylaxis, anaphylactic shock, angioedema, bronchospasm, acute tubulointerstitial nephritis, and urticaria [see Warnings and Precautions (5.3), Adverse Reactions (6)].

• Proton pump inhibitors (PPIs), including Pantoprazole Sodium for Injection, are contraindicated in patients receiving rilpivirine-containing products [see Drug Interactions (7)].

5 WARNINGS AND PRECAUTIONS

5.1 Presence of Gastric Malignancy

In adults, symptomatic response to therapy with Pantoprazole Sodium for Injection does not preclude the presence of gastric malignancy. Consider additional follow-up and diagnostic testing in adult patients who have a suboptimal response or an early symptomatic relapse after completing treatment with a PPI. In older patients, also consider an endoscopy.

5.2 Injection Site Reactions

Thrombophlebitis was associated with the administration of another intravenous pantoprazole sodium product.

5.3 Acute Tubulointerstitial Nephritis

Acute tubulointerstitial nephritis (TIN) has been observed in patients taking PPIs and may occur at any point during PPI therapy. Patients may present with varying signs and symptoms from symptomatic hypersensitivity reactions to non-specific symptoms of decreased renal function (e.g., malaise, nausea, anorexia). In reported case series, some patients were diagnosed on biopsy and in the absence of extra-renal manifestations (e.g., fever, rash or arthralgia). Discontinue Pantoprazole Sodium for Injection and evaluate patients with suspected acute TIN [see Contraindications (4)].

5.4 Clostridium difficile-Associated Diarrhea

Published observational studies suggest that PPI therapy like Pantoprazole Sodium for Injection may be associated with an increased risk of Clostridium difficile-associated diarrhea, especially in hospitalized patients. This diagnosis should be considered for diarrhea that does not improve [see Adverse Reactions (6.2)].

Patients should use the lowest dose and shortest duration of PPI therapy appropriate to the condition being treated.

5.5 Bone Fracture

Several published observational studies suggest that PPI therapy may be associated with an increased risk for osteoporosis-related fractures of the hip, wrist, or spine. The risk of fracture was increased in patients who received high-dose, defined as multiple daily doses, and long-term PPI therapy (a year or longer). Patients should use the lowest dose and shortest duration of PPI therapy appropriate to the condition being treated. Patients at risk for osteoporosis-related fractures should be managed according to established treatment guidelines [see Dosage and Administration (2.2, 2.4) and Adverse Reactions (6)].

5.6 Severe Cutaneous Adverse Reactions

Severe cutaneous adverse reactions, including Stevens-Johnson syndrome (SJS) and toxic epidermal necrolysis (TEN), drug reaction with eosinophilia and systemic symptoms (DRESS), and acute generalized exanthematous pustulosis (AGEP) have been reported in association with the use of PPIs [see Adverse Reactions (6.2)]. Discontinue Pantoprazole Sodium for Injection at the first signs or symptoms of severe cutaneous adverse reactions or other signs of hypersensitivity and consider further evaluation.

5.7 Cutaneous and Systemic Lupus Erythematosus

Cutaneous lupus erythematosus (CLE) and systemic lupus erythematosus (SLE) have been reported in patients taking PPIs, including pantoprazole sodium. These events have occurred as both new onset and an exacerbation of existing autoimmune disease. The majority of PPI-induced lupus erythematous cases were CLE.

The most common form of CLE reported in patients treated with PPIs was subacute CLE (SCLE) and occurred within weeks to years after continuous drug therapy in patients ranging from infants to the elderly. Generally, histological findings were observed without organ involvement.

Systemic lupus erythematosus (SLE) is less commonly reported than CLE in patients receiving PPIs. PPI associated SLE is usually milder than non-drug induced SLE. Onset of SLE typically occurred within days to years after initiating treatment primarily in patients ranging from young adults to the elderly. The majority of patients presented with rash; however, arthralgia and cytopenia were also reported.

Avoid administration of PPIs for longer than medically indicated. If signs or symptoms consistent with CLE or SLE are noted in patients receiving Pantoprazole Sodium for Injection, discontinue the drug and refer the patient to the appropriate specialist for evaluation. Most patients improve with discontinuation of the PPI alone in 4 to 12 weeks. Serological testing (e.g. ANA) may be positive and elevated serological test results may take longer to resolve than clinical manifestations.

5.8 Hepatic Effects

Mild, transient transaminase elevations have been observed in clinical studies. The clinical significance of this finding in a large population of subjects administered intravenous pantoprazole sodium is unknown [see Adverse Reactions (6.1)].

5.9 Hypomagnesemia and Mineral Metabolism

Hypomagnesemia, symptomatic and asymptomatic, has been reported rarely in patients treated with PPIs for at least three months, and in most cases after a year of therapy. Serious adverse reactions include tetany, arrhythmias, and seizures. Hypomagnesemia may lead to hypocalcemia and/or hypokalemia and may exacerbate underlying hypocalcemia in at-risk patients. In most patients, treatment of hypomagnesemia required magnesium replacement and discontinuation of the PPI.

For patients expected to be on prolonged treatment or who take PPIs with medications such as digoxin or drugs that may cause hypomagnesemia (e.g., diuretics), healthcare professionals may consider monitoring magnesium levels prior to initiation of PPI treatment and periodically [see Adverse Reactions (6.2)].

Consider monitoring magnesium and calcium levels prior to initiation of Pantoprazole Sodium for Injection and periodically while on treatment in patients with a preexisting risk of hypocalcemia (e.g., hypoparathyroidism). Supplement with magnesium and/or calcium as necessary. If hypocalcemia is refractory to treatment, consider discontinuing the PPI.

5.10 Fundic Gland Polyps

PPI use is associated with an increased risk of fundic gland polyps that increases with long-term use, especially beyond one year. Most PPI users who developed fundic gland polyps were asymptomatic and fundic polyps were identified incidentally on endoscopy. Use the shortest duration of PPI therapy appropriate to the condition being treated.

5.11 Interference with Investigations for Neuroendocrine Tumors

Serum chromogranin A (CgA) levels increase secondary to drug-induced decreases in gastric acidity. The increased CgA level may cause false positive results in diagnostic investigations for neuroendocrine tumors. Healthcare providers should temporarily stop Pantoprazole Sodium for Injection treatment at least 14 days before assessing CgA levels and consider repeating the test if initial CgA levels are high. If serial tests are performed (e.g. for monitoring), the same commercial laboratory should be used for testing, as reference ranges between tests may vary [see Clinical Pharmacology (12.2)].

5.12 Interference with Urine Screen for THC

Pantoprazole sodium may produce a false-positive urine screen for THC (tetrahydrocannabinol) [see Drug Interactions (7)].

5.13 Concomitant Use of Pantoprazole Sodium for Injection with Methotrexate

Literature suggests that concomitant use of PPIs with methotrexate (primarily at high dose; see methotrexate prescribing information) may elevate and prolong serum levels of methotrexate and/or its metabolite, possibly leading to methotrexate toxicities. In high-dose methotrexate administration, a temporary withdrawal of the PPI may be considered in some patients [see Drug Interactions (7)].

6 ADVERSE REACTIONS

The following serious adverse reactions are described below and elsewhere in labeling:

• Injection Site Reactions [see Warnings and Precautions (5.2)]

• Acute Tubulointerstitial Nephritis [see Warnings and Precautions (5.3)]

• Clostridium difficile-Associated Diarrhea [see Warnings and Precautions (5.4)]

• Bone Fracture [see Warnings and Precautions (5.5)]

• Severe Cutaneous Adverse Reactions [See Warnings and Precautions (5.6)]

• Cutaneous and Systemic Lupus Erythematosus [see Warnings and Precautions (5.7)]

• Hepatic Effects [see Warnings and Precautions (5.8)]

• Hypomagnesemia and Mineral Metabolism [see Warnings and Precautions (5.9)]

• Fundic Gland Polyps[see Warnings and Precautions (5.10)]

6.1 Clinical Trials Experience

Because clinical trials are conducted under widely varying conditions, adverse reaction rates observed in the clinical trials of a drug cannot be directly compared to rates in the clinical trials of another drug and may not reflect the rates observed in clinical practice.

The safety of Pantoprazole Sodium for Injection has been established from adequate and well-controlled studies of another intravenous pantoprazole sodium product [see Clinical Studies (14)]. Below is a display of the adverse reactions of pantoprazole sodium in these adequate and well-controlled studies.

Gastroesophageal Reflux Disease (GERD)

Safety in nine randomized comparative US clinical trials in patients with GERD included 1,473 patients on oral pantoprazole (20 mg or 40 mg), 299 patients on an H2-receptor antagonist, 46 patients on another PPI, and 82 patients on placebo. The most frequently occurring adverse reactions are listed in Table 1.

The number of patients treated in comparative studies with intravenous pantoprazole sodium is limited; however, the adverse reactions seen were similar to those seen in the oral studies. Thrombophlebitis was the only new adverse reaction identified with intravenous pantoprazole sodium.

Table 1: Adverse Reactions Reported in Clinical Trials of Adult Patients with GERD at a Frequency of >2%

 | Oral Pantoprazole Sodium (n=1473) % | Comparators (n=345) % | Placebo (n=82) %
Headache | 12.2 | 12.8 | 8.5
Diarrhea | 8.8 | 9.6 | 4.9
Nausea | 7 | 5.2 | 9.8
Abdominal pain | 6.2 | 4.1 | 6.1
Vomiting | 4.3 | 3.5 | 2.4
Flatulence | 3.9 | 2.9 | 3.7
Dizziness | 3 | 2.9 | 1.2
Arthralgia | 2.8 | 1.4 | 1.2

Additional adverse reactions that were reported for oral pantoprazole sodium in US clinical trials with a frequency of 2% or less are listed below by body system:

Body as a Whole: allergic reaction, fever, photosensitivity reaction, facial edema, thrombophlebitis (intravenous only)

Gastrointestinal: constipation, dry mouth, hepatitis
Hematologic: leukopenia (reported in ex-US clinical trials only), thrombocytopenia

Metabolic/Nutritional: elevated CPK (creatine phosphokinase), generalized edema, elevated triglycerides, liver function tests abnormal

Musculoskeletal: myalgia

Nervous: depression, vertigo

Skin and Appendages: urticaria, rash, pruritus

Special Senses: blurred vision

Zollinger-Ellison Syndrome

In clinical studies of Zollinger-Ellison Syndrome, adverse reactions reported in 35 patients administered oral pantoprazole doses of 80 mg to 240 mg per day for up to 2 years were similar to those reported in adult patients with GERD.

6.2 Postmarketing Experience

The following adverse reactions have been identified during postapproval use of other pantoprazole sodium products. Because these reactions are reported voluntarily from a population of uncertain size, it is not always possible to reliably estimate their frequency or establish a causal relationship to drug exposure.

These adverse reactions are listed below by body system:

General Disorders and Administration Conditions: asthenia, fatigue, malaise

Immune System Disorders: anaphylaxis (including anaphylactic shock), systemic lupus erythematosus

Investigations: weight changes

Skin and Subcutaneous Tissue Disorders: severe dermatologic reactions (some fatal), including erythema multiforme, SJS/TEN, DRESS, AGEP [see Warnings and Precautions (5.6)], and angioedema (Quincke's edema) and cutaneous lupus erythematosus

Musculoskeletal Disorders: rhabdomyolysis, bone fracture

Renal and Genitourinary Disorders: interstitial nephritis, erectile dysfunction

Hepatobiliary Disorders: hepatocellular damage leading to jaundice and hepatic failure

Psychiatric Disorder: hallucinations, confusion, insomnia, somnolence

Metabolism and Nutritional Disorders: hypomagnesemia, hypocalcemia, hypokalemia [see Warnings and Precautions (5.9)], hyponatremia

Infections and Infestations: Clostridium difficile-associated diarrhea

Hematologic: pancytopenia, agranulocytosis

Nervous: ageusia, dysgeusia

Gastrointestinal Disorders: fundic gland polyps

7 DRUG INTERACTIONS

Table 2 includes drugs with clinically important drug interactions and interaction with diagnostics when administered concomitantly with Pantoprazole Sodium for Injection and instructions for preventing or managing them.

Consult the labeling of concomitantly used drugs to obtain further information about interactions with PPIs.

Table 2: Clinically Relevant Interactions Affecting Drugs Co-Administered with Pantoprazole Sodium for Injection and Interaction with Diagnostics

Antiretrovirals
Clinical Impact: | The effect of PPIs on antiretroviral drugs is variable. The clinical importance and the mechanisms behind these interactions are not always known.; • Decreased exposure of some antiretroviral drugs (e.g., rilpivirine, atazanavir, and nelfinavir) when used concomitantly with pantoprazole may reduce antiviral effect and promote the development of drug resistance.; • Increased exposure of other antiretroviral drugs (e.g., saquinavir) when used concomitantly with pantoprazole may increase toxicity [see Clinical Pharmacology (12.3)].; • There are other antiretroviral drugs which do not result in clinically relevant interactions with pantoprazole.
Intervention: | Rilpivirine-containing products: Concomitant use with Pantoprazole Sodium for Injection is contraindicated [see Contraindications (4)]. See prescribing information.; Atazanavir: See prescribing information for atazanavir for dosing information.; Nelfinavir: Avoid concomitant use with Pantoprazole Sodium for Injection. See prescribing information for nelfinavir.; Saquinavir: See the prescribing information for saquinavir and for monitoring of potential saquinavir-related toxicities.; Other antiretrovirals: See prescribing information for specific antiretroviral drugs.
Warfarin
Clinical Impact: | Increased INR and prothrombin time in patients receiving PPIs, including pantoprazole, and warfarin concomitantly. Increases in INR and prothrombin time may lead to abnormal bleeding and even death.
Intervention: | Monitor INR and prothrombin time and adjust the dose of warfarin, if needed, to maintain the target INR range. See prescribing information for warfarin.
Clopidogrel
Clinical Impact: | Concomitant administration of pantoprazole and clopidogrel in healthy subjects had no clinically important effect on exposure to the active metabolite of clopidogrel-induced platelet inhibition [see Clinical Pharmacology (12.3)].
Intervention: | No dose adjustment of clopidogrel is necessary when administered with an approved dose of Pantoprazole Sodium for Injection.

Methotrexate
Clinical Impact: | Concomitant use of PPIs with methotrexate (primarily at high dose) may elevate and prolong serum concentrations of methotrexate and/or its metabolite hydroxymethotrexate, possibly leading to methotrexate toxicities. No formal drug interaction studies of high-dose methotrexate with PPIs have been conducted [see Warnings and Precautions (5.13)].
Intervention: | A temporary withdrawal of Pantoprazole Sodium for Injection may be considered in some patients receiving high-dose methotrexate.
Drugs Dependent on Gastric pH for Absorption (e.g., iron salts, erlotinib, dasatinib, nilotinib, mycophenoloate mofetil, ketoconazole/itraconazole)
Clinical Impact: | Pantoprazole can reduce the absorption of other drugs due to its effect on reducing intragastric acidity
Intervention: | Mycophenolate mofetil (MMF): Co-administration of pantoprazole sodium in healthy subjects and in transplant patients receiving MMF has been reported to reduce the exposure to the active metabolite, mycophenolic acid (MPA), possibly due to a decrease in MMF solubility at an increased gastric pH [see Clinical Pharmacology (12.3)]. The clinical relevance of reduced MPA exposure on organ rejection has not been established in transplant patients receiving Pantoprazole Sodium for Injection and MMF. Use Pantoprazole Sodium for Injection with caution in transplant patients receiving MMF [see Clinical Pharmacology (12.3)].; See the prescribing information for other drugs dependent on gastric pH for absorption.
Interactions with Investigations of Neuroendocrine Tumors
Clinical Impact: | CgA levels increase secondary to PPI-induced decreases in gastric acidity. The increased CgA level may cause false positive results in diagnostic investigations for neuroendocrine tumors [see Warnings and Precautions (5.11), Clinical Pharmacology (12.2)].
Intervention: | Temporarily stop Pantoprazole Sodium for Injection treatment at least 14 days before assessing CgA levels and consider repeating the test if initial CgA levels are high. If serial tests are performed (e.g. for monitoring), the same commercial laboratory should be used for testing, as reference ranges between tests may vary.
False Positive Urine Tests for THC
Clinical Impact: | There have been reports of false positive urine screening tests for tetrahydrocannabinol (THC) in patients receiving PPIs, including pantoprazole sodium [see Warnings and Precautions (5.12)].
Intervention: | An alternative confirmatory method should be considered to verify positive results.

8 USE IN SPECIFIC POPULATIONS

8.1 Pregnancy

Risk Summary

Available data from published observational studies did not demonstrate an association of major malformations or other adverse pregnancy outcomes with pantoprazole (see Data).

In animal reproduction studies, no evidence of adverse development outcomes was observed with pantoprazole. Reproduction studies have been performed in rats at intravenous doses up to 20 mg/kg/day (4 times the recommended human dose) and rabbits at intravenous doses up to 15 mg/kg/day (6 times the recommended human dose) with administration of pantoprazole during organogenesis in pregnant animals and have revealed no evidence of harm to the fetus due to pantoprazole in this study (see Data).

A pre- and postnatal development toxicity study in rats with additional endpoints to evaluate the effect on bone development was performed with pantoprazole sodium. Oral pantoprazole doses of 5, 15, and 30 mg/kg/day (approximately 1, 3, and 6 times the human dose of 40 mg/day) were administered to pregnant females from gestation day (GD) 6 through lactation day (LD) 21. Changes in bone morphology were observed in pups exposed to pantoprazole in utero and through milk during the period of lactation as well as by oral dosing from postnatal day (PND) 4 through PND 21 [see Use in Specific Populations (8.4)]. There were no drug-related findings in maternal animals. Advise pregnant women of the potential risk of fetal harm.

The estimated background risk of major birth defects and miscarriage for the indicated population is unknown. All pregnancies have a background risk of birth defect, loss or other adverse outcomes. In the U.S. general population, the estimated background risk of major birth defects and miscarriage in the clinically recognized pregnancies is 2 to 4% and 15 to 20%, respectively.

Data

Human Data

Available data from published observational studies failed to demonstrate an association of adverse pregnancy-related outcomes and pantoprazole use. Methodological limitations of these observational studies cannot definitely establish or exclude any drug-associated risk during pregnancy. In a prospective study by the European Network of Teratology Information Services, outcomes from a group of 53 pregnant women administered median daily doses of 40 mg pantoprazole were compared to a control group of 868 pregnant women who did not take any proton pump inhibitors (PPIs). There was no difference in the rate of major malformations between women exposed to PPIs and the control group, corresponding to a Relative Risk (RR)= 0.55, [95% Confidence Interval (CI) 0.08-3.95]. In a population-based retrospective cohort study covering all live births in Denmark from 1996 to 2008, there was no significant increase in major birth defects during analysis of first trimester exposure to pantoprazole in 549 live births. A meta-analysis that compared 1,530 pregnant women exposed to PPIs in at least the first trimester with 133,410 unexposed pregnant women showed no significant increases in risk for congenital malformations or spontaneous abortion with exposure to PPIs (for major malformations OR=1.12 [95% CI 0.86-1.45] and for spontaneous abortions OR=1.29 [95% CI 0.84-1.97]).

Animal Data

Reproduction studies have been performed in rats at intravenous pantoprazole doses up to 20 mg/kg/day (4 times the recommended human dose based on body surface area) and rabbits at intravenous doses up to 15 mg/kg/day (6 times the recommended human dose based on body surface area) with administration of pantoprazole sodium during organogenesis in pregnant animals and have revealed no evidence of impaired fertility or harm to the fetus due to pantoprazole.

A pre- and postnatal development toxicity study in rats with additional endpoints to evaluate the effect on bone development was performed with pantoprazole sodium. Oral pantoprazole doses of 5, 15, and 30 mg/kg/day (approximately 1, 3, and 6 times the human dose of 40 mg/day on a body surface area basis) were administered to pregnant females from gestation day (GD) 6 through lactation day (LD) 21. On postnatal day (PND) 4 through PND 21, the pups were administered oral doses at 5, 15, and 30 mg/kg/day (approximately 1, 2.3, and 3.2 times the exposure (AUC) in humans at a dose of 40 mg). There were no drug-related findings in maternal animals. During the preweaning dosing phase (PND 4 to 21) of the pups, there were increased mortality and/or moribundity and decreased body weight and body weight gain at 5 mg/kg/day (approximately equal exposures (AUC) in humans receiving the 40 mg dose) and higher doses. On PND 21, decreased mean femur length and weight and changes in femur bone mass and geometry were observed in the offspring at 5 mg/kg/day (approximately equal exposures (AUC) in humans at the 40 mg dose) and higher doses. The femur findings included lower total area, bone mineral content and density, periosteal and endosteal circumference, and cross-sectional moment of inertia. There were no microscopic changes in the distal femur, proximal tibia, or stifle joints.

Changes in bone parameters were partially reversible following a recovery period, with findings on PND 70 limited to lower femur metaphysis cortical/subcortical bone mineral density in female pups at 5 mg/kg/day (approximately equal exposures (AUC) in humans at the 40 mg dose) and higher doses.

8.2 Lactation

Risk Summary

The limited data from a single case reports the presence of pantoprazole in human breast milk. There were no effects on the breastfed infant (see Data). There are no data on pantoprazole effects on milk production.

The developmental and health benefits of breastfeeding should be considered along with the mother’s clinical need for pantoprazole and any potential adverse effects on the breastfed child from pantoprazole or from the underlying maternal condition.

Data

The breast milk of a 42-year-old woman receiving 40 mg of oral pantoprazole, at 10 months postpartum, was studied for 24 hours, to demonstrate low levels of pantoprazole present in the breast milk. Pantoprazole was detectable in milk only 2 and 4 hours after the dose with milk levels of approximately 36 mcg/L and 24 mcg/L, respectively. A milk-to-plasma ratio of 0.022 was observed at 2 hours after drug administration. Pantoprazole was not detectable (less than 10 mcg/L) in milk at 6, 8 and 24 hours after the dose. The relative dose to the infant was estimated to be 7.3 mcg of pantoprazole, which is equivalent to 0.14% of the weight-adjusted maternal dose. No adverse events in the infant were reported by the mother.

8.4 Pediatric Use

The safety and effectiveness of Pantoprazole Sodium for Injection have not been established in pediatric patients.

Animal Toxicity Data

In a pre- and post-natal development study in rats, the pups were administered oral doses of pantoprazole at 5, 15, and 30 mg/kg/day on postnatal day (PND 4) through PND 21, in addition to lactational exposure through milk. On PND 21, decreased mean femur length and weight and changes in femur bone mass and geometry were observed in the offspring at 5 mg/kg/day and higher doses. Changes in bone parameters were partially reversible following a recovery period [see Use in Specific Populations (8.1)].

In neonatal/juvenile animals (rats and dogs) toxicities were similar to those observed in adult animals including gastric alterations, decreases in red cell mass, increases in lipids, enzyme induction and hepatocellular hypertrophy. An increased incidence of eosinophilic chief cells in adult and neonatal/juvenile rats, and atrophy of chief cells in adult rats and in neonatal/juvenile dogs, was observed in the fundic mucosa of stomachs in repeated-dose studies. Full to partial recovery of these effects were noted in animals of both age groups following a recovery period.

8.5 Geriatric Use

Of 286 patients in clinical studies of intravenous pantoprazole sodium in patients with GERD and a history of EE, 86 (43%) were 65 years of age and over. No overall differences in safety or effectiveness were observed between these subjects and younger subjects, and other reported clinical experience with oral pantoprazole sodium has not identified differences in responses between the elderly and younger patients, but greater sensitivity of some older individuals cannot be ruled out.

10 OVERDOSAGE

Experience in patients taking very high doses of pantoprazole (greater than 240 mg) is limited. Adverse reactions seen in spontaneous reports of overdose generally reflect the known safety profile of pantoprazole.

Pantoprazole is not removed by hemodialysis. In case of overdose, treatment should be symptomatic and supportive.

Single intravenous doses of pantoprazole at 378, 230, and 266 mg/kg (38, 46, and 177 times the recommended human dose based on body surface area) were lethal to mice, rats and dogs, respectively. The symptoms of acute toxicity were hypoactivity, ataxia, hunched sitting, limb-splay, lateral position, segregation, absence of ear reflex, and tremor.

11 DESCRIPTION

The active ingredient in Pantoprazole Sodium for Injection, a PPI, is a substituted benzimidazole, sodium 5-(difluoromethoxy)-2-[[(3,4-dimethoxy-2-pyridyl)methyl]sulfinyl]-1H-benzimidazole sesquihydrate, a compound that inhibits gastric acid secretion. Its empirical formula is C16H14F2N3NaO4S•1.5 H2O, with a molecular weight of 432.37. The structural formula is:

Pantoprazole sodium is a white to off-white crystalline powder and is racemic. Pantoprazole sodium is freely soluble in water, very slightly soluble in phosphate buffer at pH 7.4, and practically insoluble in n-hexane. The stability of the compound in aqueous solution is pH-dependent. The rate of degradation increases with decreasing pH. The reconstituted solution of Pantoprazole Sodium for Injection is in the pH range 9.5 to 11.5.

Pantoprazole Sodium for Injection is supplied for intravenous administration as a sterile lyophilized powder in a single-dose clear glass vial fitted with a rubber stopper and crimp seal. Each vial contains 40 mg pantoprazole (equivalent to 45.1 mg of pantoprazole sodium), and sodium hydroxide to adjust pH.

12 CLINICAL PHARMACOLOGY

12.1 Mechanism of Action

Pantoprazole is a PPI that suppresses the final step in gastric acid production by covalently binding to the (H^+, K^+)-ATPase enzyme system at the secretory surface of the gastric parietal cell. This effect leads to inhibition of both basal and stimulated gastric acid secretion irrespective of the stimulus. The binding to the (H^+, K^+)-ATPase results in a duration of antisecretory effect that persists longer than 24 hours for all doses tested (20 mg to 120 mg).

12.2 Pharmacodynamics

Antisecretory Activity

The magnitude and time course for inhibition of pentagastrin-stimulated acid output (PSAO) by single intravenous doses (20 to 120 mg) of pantoprazole were assessed in a single-dose, open-label, placebo-controlled, dose-response study. The results of this study are shown in Table 3. Healthy subjects received a continuous infusion for 25 hours of pentagastrin (PG) at 1 mcg/kg/hour, a dose known to produce submaximal gastric acid secretion. The placebo group showed a sustained, continuous acid output for 25 hours, validating the reliability of the testing model. Intravenous administration of pantoprazole sodium had an onset of antisecretory activity within 15 to 30 minutes of administration.

Intravenous doses of 20 to 80 mg of pantoprazole substantially reduced the 24-hour cumulative PSAO in a dose-dependent manner, despite a short plasma elimination half-life. Complete suppression of PSAO was achieved with 80 mg within approximately 2 hours and no further significant suppression was seen with 120 mg. The duration of action of intravenous pantoprazole sodium was 24 hours.

Table 3: Gastric Acid Output (mEq/hr, Mean ± SD) and Percent Inhibition* (Mean ± SD) of Pentagastrin-Stimulated Acid Output Over 24 Hours Following a Single Dose of Another Intravenous Pantoprazole Sodium† Product in Healthy Subjects

 | 2 hours |  | 4 hours |  | 12 hours |  | 24 hours
Treatment Dose | Acid; Output | % Inhibition | Acid; Output | % Inhibition | Acid; Output | % Inhibition | Acid; Output | % Inhibition
0 mg; (Placebo, n=4) | 39 ± 21 | NA | 26 ± 14 | NA | 32 ± 20 | NA | 38 ± 24 | NA
20 mg; (n=4-6) | 13 ± 18 | 47 ± 27 | 6 ± 8 | 83 ± 21 | 20 ± 20 | 54 ± 44 | 30 ± 23 | 45 ± 43
40 mg; (n=8) | 5 ± 5 | 82 ± 11 | 4 ± 4 | 90 ± 11 | 11 ± 10 | 81 ± 13 | 16 ± 12 | 52 ± 36
80 mg; (n=8) | 0.1 ± 0.2 | 96 ± 6 | 0.3 ± 0.4 | 99 ± 1 | 2 ± 2 | 90 ± 7 | 7 ± 4 | 63 ± 18

NA = not applicable.
* Compared to individual subject baseline prior to treatment with intravenous pantoprazole sodium.
† Inhibition of gastric acid output and the percent inhibition of stimulated acid output in response to intravenous pantoprazole sodium may be higher after repeated doses.

In one study of gastric pH in healthy subjects, pantoprazole was administered orally (40 mg enteric coated tablets) or intravenously (40 mg) once daily for 5 days and pH was measured for 24 hours following the fifth dose. The outcome measure was median percent of time that pH was ≥ 4 and the results were similar for intravenous and oral medications; however, the clinical significance of this parameter is unknown.

Serum Gastrin Effects

Serum gastrin concentrations were assessed in two placebo-controlled studies.

In a 5-day study of oral pantoprazole with 40 and 60 mg doses in healthy subjects, following the last dose on day 5, median 24-hour serum gastrin concentrations were elevated by 3 to 4 fold compared to placebo in both 40 and 60 mg dose groups. However, by 24 hours following the last dose, median serum gastrin concentrations for both groups returned to normal levels.

In another placebo-controlled, 7-day study of 40 mg intravenous or oral pantoprazole in patients with GERD and a history of EE, the mean serum gastrin concentration increased approximately 50% from baseline and as compared with placebo, but remained within the normal range.

During 6 days of repeated administration of intravenous pantoprazole sodium in patients with ZE Syndrome, consistent changes of serum gastrin concentrations from baseline were not observed.

Enterochromaffin-Like (ECL) Cell Effects

There are no data available on the effects of intravenous pantoprazole sodium on ECL cells.

In a nonclinical study in Sprague-Dawley rats, lifetime exposure (24 months) to oral pantoprazole at doses of 0.5 to 200 mg/kg/day resulted in dose-related increases in gastric ECL-cell proliferation and gastric neuroendocrine (NE)-cell tumors. Gastric NE-cell tumors in rats may result from chronic elevation of serum gastrin concentrations. The high density of ECL cells in the rat stomach makes this species highly susceptible to the proliferative effects of elevated gastrin concentrations produced by PPIs. However, there were no observed elevations in serum gastrin following the administration of oral pantoprazole at a dose of 0.5 mg/kg/day. In a separate study, a gastric NE-cell tumor without concomitant ECL-cell proliferative changes was observed in 1 female rat following 12 months of dosing with oral pantoprazole at 5 mg/kg/day and a 9 month off-dose recovery [see Nonclinical Toxicology (13.1)].

Endocrine Effects

In a clinical pharmacology study, pantoprazole 40 mg given orally once daily for 2 weeks had no effect on the levels of the following hormones: cortisol, testosterone, triiodothyronine (T3), thyroxine (T4), thyroid-stimulating hormone, thyronine-binding protein, parathyroid hormone, insulin, glucagon, renin, aldosterone, follicle-stimulating hormone, luteinizing hormone, prolactin and growth hormone.

12.3 Pharmacokinetics

Pantoprazole peak serum concentration (Cmax) and area under the serum concentration-time curve (AUC) increase in a manner proportional to intravenous doses of pantoprazole from 10 mg to 80 mg. Pantoprazole does not accumulate and its pharmacokinetics are unaltered with multiple daily dosing. Following the administration of intravenous pantoprazole sodium, the serum concentration of pantoprazole declines biexponentially with a terminal elimination half-life of approximately one hour. In CYP2C19 extensive metabolizers [see Clinical Pharmacology (12.5)] with normal liver function receiving a 40 mg intravenous dose of pantoprazole by constant rate over 15 minutes, the peak concentration (Cmax) is 5.52 ± 1.42 mcg/mL and the total area under the plasma concentration versus time curve (AUC) is 5.4 ± 1.5 mcg•hr/mL. The total clearance is 7.6 to 14 L/h.

Distribution

The apparent volume of distribution of pantoprazole is approximately 11 to 23.6 L, distributing mainly in extracellular fluid. The serum protein binding of pantoprazole is about 98%, primarily to albumin.

Elimination

Metabolism

Pantoprazole is extensively metabolized in the liver through the cytochrome P450 (CYP) system. Pantoprazole metabolism is independent of the route of administration (intravenous or oral). The main metabolic pathway is demethylation, by CYP2C19, with subsequent sulfation; other metabolic pathways include oxidation by CYP3A4. There is no evidence that any of the pantoprazole metabolites have significant pharmacologic activity. CYP2C19 displays a known genetic polymorphism due to its deficiency in some sub-populations (e.g., 3% of Caucasians and African-Americans and 17 to 23% of Asians). Although these sub-populations of slow pantoprazole metabolizers have elimination half-life values from 3.5 to 10 hours, they still have minimal accumulation (23% or less) with once daily dosing.

Excretion

After administration of a single intravenous dose of ^14C-labeled pantoprazole sodium to healthy, extensive CYP2C19 metabolizers, approximately 71% of the dose was excreted in the urine with 18% excreted in the feces through biliary excretion. There was no renal excretion of unchanged pantoprazole.

Specific Populations

Geriatric Patients

After repeated intravenous administration in elderly subjects (65 to 76 years of age), the AUC and elimination half-life values of pantoprazole were similar to those observed in younger subjects.

Male and Female Patients

After oral administration there was a modest increase in the AUC and Cmax of pantoprazole in women compared to men. However, weight-normalized clearance values are similar in women and men.

Patients with Renal Impairment

In patients with severe renal impairment, pharmacokinetic parameters for pantoprazole were similar to those of healthy subjects.

Patients with Hepatic Impairment

In patients with mild to severe hepatic impairment (Child-Pugh Class A to C), maximum pantoprazole concentrations increased only slightly (1.5-fold) relative to healthy subjects when pantoprazole sodium was administered orally. Although serum half-life values increased to 7 to 9 hours and AUC values increased by 5- to 7-fold in hepatic-impaired patients, these increases were no greater than those observed in CYP2C19 poor metabolizers, where no dosage adjustment is warranted. These pharmacokinetic changes in hepatic-impaired patients result in minimal drug accumulation following once-daily, multiple-dose administration. Oral pantoprazole doses higher than 40 mg per day have not been studied in hepatically impaired patients.

Drug Interaction Studies

Effect of Other Drugs on Pantoprazole

Pantoprazole is metabolized mainly by CYP2C19 and to minor extents by CYPs 3A4, 2D6 and 2C9.

In in vivo drug-drug interaction studies with CYP2C19 substrates (diazepam [also a CYP3A4 substrate] and phenytoin [also a CYP3A4 inducer]), nifedipine, midazolam, and clarithromycin (CYP3A4 substrates), metoprolol (a CYP2D6 substrate), diclofenac, naproxen and piroxicam (CYP2C9 substrates) and theophylline (a CYP1A2 substrate) in healthy subjects, the pharmacokinetics of pantoprazole were not significantly altered.

Effect of Pantoprazole on Other Drugs

Clopidogrel

Clopidogrel is metabolized to its active metabolite in part by CYP2C19. In a crossover clinical study, 66 healthy subjects were administered clopidogrel (300 mg loading dose followed by 75 mg per day) alone and with oral pantoprazole (80 mg at the same time as clopidogrel) for 5 days. On Day 5, the mean AUC of the active metabolite of clopidogrel was reduced by approximately 14% (geometric mean ratio was 86%, with 90% CI of 79 to 93%) when pantoprazole sodium was coadministered with clopidogrel as compared to clopidogrel administered alone. Pharmacodynamic parameters were also measured and demonstrated that the change in inhibition of platelet aggregation (induced by 5 micromolar ADP) was correlated with the change in the exposure to clopidogrel active metabolite. The clinical significance of this finding is not clear.

Mycophenolate Mofetil (MMF)

Administration of oral pantoprazole 40 mg twice daily for 4 days and a single 1000 mg dose of MMF approximately one hour after the last dose of pantoprazole to 12 healthy subjects in a cross-over study resulted in a 57% reduction in the Cmax and 27% reduction in the AUC of MPA. Transplant patients receiving approximately 2000 mg per day of MMF (n=12) were compared to transplant patients receiving approximately the same dose of MMF and oral pantoprazole 40 mg per day (n=21). There was a 78% reduction in the Cmax and a 45% reduction in the AUC of MPA in patients receiving both pantoprazole sodium and MMF [see Drug Interactions (7)].

Other Drugs

In vivo studies also suggest that pantoprazole does not significantly affect the kinetics of other drugs (theophylline, diazepam [and its active metabolite, desmethyldiazepam], phenytoin, metoprolol, nifedipine, carbamazepine, midazolam, clarithromycin, diclofenac, naproxen, piroxicam and oral contraceptives [levonorgestrel/ethinyl estradiol]). In other in vivo studies, digoxin, ethanol, glyburide, antipyrine, caffeine, metronidazole, and amoxicillin had no clinically relevant interactions with pantoprazole.

Although no significant drug-drug interactions have been observed in clinical studies, the potential for significant drug-drug interactions with more than once daily dosing with high doses of pantoprazole has not been studied in poor metabolizers or individuals who are hepatically impaired.

Antacids

There was also no interaction with concomitantly administered antacids.

12.5 Pharmacogenomics

CYP2C19 displays a known genetic polymorphism due to its deficiency in some subpopulations (e.g., approximately 3% of Caucasians and African-Americans and 17% to 23% of Asians are poor metabolizers). Although these subpopulations of pantoprazole poor metabolizers have elimination half-life values of 3.5 to 10 hours in adults, they still have minimal accumulation (less than or equal to 23%) with once-daily dosing. For adult patients who are CYP2C19 poor metabolizers, no dosage adjustment is needed.

Similar to adults, pediatric patients who have the poor metabolizer genotype of CYP2C19 (CYP2C19*2/*2) exhibited greater than a 6-fold increase in AUC compared to pediatric extensive (CYP2C19*1/*1) and intermediate (CYP2C19 *1/*x) metabolizers. Poor metabolizers exhibited approximately 10-fold lower apparent oral clearance compared to extensive metabolizers.

13 NONCLINICAL TOXICOLOGY

13.1 Carcinogenesis, Mutagenesis, Impairment of Fertility

In a 24-month carcinogenicity study, Sprague-Dawley rats were treated orally with pantoprazole doses of 0.5 to 200 mg/kg/day, about 0.1 to 40 times the exposure on a body surface area basis of a 50-kg person dosed at 40 mg/day. In the gastric fundus, treatment with 0.5 to 200 mg/kg/day produced enterochromaffin-like (ECL) cell hyperplasia and benign and malignant neuroendocrine cell tumors in a dose-related manner. In the forestomach, treatment with 50 and 200 mg/kg/day (about 10 and 40 times the recommended human dose on a body surface area basis) produced benign squamous cell papillomas and malignant squamous cell carcinomas. Rare gastrointestinal tumors associated with pantoprazole treatment included an adenocarcinoma of the duodenum with 50 mg/kg/day and benign polyps and adenocarcinomas of the gastric fundus with 200 mg/kg/day. In the liver, treatment with 0.5 to 200 mg/kg/day produced dose-related increases in the incidences of hepatocellular adenomas and carcinomas. In the thyroid gland, treatment with 200 mg/kg/day produced increased incidences of follicular cell adenomas and carcinomas for both male and female rats.

In a 24-month carcinogenicity study, Fischer 344 rats were treated orally with pantoprazole doses of 5 to 50 mg/kg/day, approximately 1 to 10 times the recommended human dose based on body surface area. In the gastric fundus, treatment at 5 to 50 mg/kg/day produced enterochromaffin-like (ECL) cell hyperplasia and benign and malignant neuroendocrine cell tumors. Dose selection for this study may not have been adequate to comprehensively evaluate the carcinogenic potential of pantoprazole.

In a 24-month carcinogenicity study, B6C3F1 mice were treated orally with pantoprazole doses of 5 to 150 mg/kg/day, 0.5 to 15 times the recommended human dose based on body surface area. In the liver, treatment at 150 mg/kg/day produced increased incidences of hepatocellular adenomas and carcinomas in female mice. Treatment at 5 to 150 mg/kg/day also produced gastric fundic ECL cell hyperplasia.

A 26-week p53 +/- transgenic mouse carcinogenicity study was not positive.

Pantoprazole was positive in the in vitro human lymphocyte chromosomal aberration assays, in one of two mouse micronucleus tests for clastogenic effects, and in the in vitro Chinese hamster ovarian cell/HGPRT forward mutation assay for mutagenic effects. Equivocal results were observed in the in vivo rat liver DNA covalent binding assay. Pantoprazole was negative in the in vitro Ames mutation assay, the in vitro unscheduled DNA synthesis (UDS) assay with rat hepatocytes, the in vitro AS52/GPT mammalian cell-forward gene mutation assay, the in vitro thymidine kinase mutation test with mouse lymphoma L5178Y cells, and the in vivo rat bone marrow cell chromosomal aberration assay.

There were no effects on fertility or reproductive performance when pantoprazole was given at oral doses up to 500 mg/kg/day in male rats (98 times the recommended human dose based on body surface area) and 450 mg/kg/day in female rats (88 times the recommended human dose based on body surface area).

14 CLINICAL STUDIES

The safety and efficacy of Pantoprazole Sodium for Injection have been established based on adequate and well-controlled adult studies of another intravenous pantoprazole sodium product in GERD associated with a history of EE and pathological hypersecretory conditions, including Zollinger-Ellison syndrome. Below is a display of the results of these adequate and well-controlled studies of pantoprazole sodium in these conditions.

14.1 Gastroesophageal Reflux Disease (GERD) Associated with a History of Erosive Esophagitis

A multicenter, double-blind, two-period placebo-controlled study was conducted to assess the ability of pantoprazole sodium to maintain gastric acid suppression in patients switched from the oral dosage form to the intravenous dosage form. GERD patients (n=65, 26 to 64 years; 35 female; 9 Black, 11 Hispanic, 44 White, 1 other) with a history of EE were randomized to receive either 20 or 40 mg of oral pantoprazole once per day for 10 days (period 1), and then were switched in period 2 to either daily intravenous pantoprazole sodium or placebo for 7 days, matching their respective dose level from period 1. Patients were administered all test medication with a light meal. Maximum acid output (MAO) and basal acid output (BAO) were determined 24 hours following the last day of oral medication (day 10), the first day (day 1) of intravenous administration and the last day of intravenous administration (day 7). MAO was estimated from a 1 hour continuous collection of gastric contents following subcutaneous injection of 6 mcg/kg of pentagastrin.

This study demonstrated that, after 10 days of repeated oral administration followed by 7 days of intravenous administration, the oral and intravenous dosage forms of pantoprazole 40 mg are similar in their ability to suppress MAO and BAO in patients with GERD and a history of erosive esophagitis (see Table 4). Also, patients on oral pantoprazole sodium who were switched to intravenous placebo experienced a significant increase in acid output within 48 hours of their last oral dose (see Table 4). However, at 48 hours after their last oral dose, patients treated with intravenous pantoprazole sodium had a significantly lower mean basal acid output (see Table 4) than those treated with placebo.

Table 4: Antisecretory Effects (mEq/h) of 40 mg Intravenous Pantoprazole Sodium and 40 mg Oral Pantoprazole in GERD Patients with a History of Erosive Esophagitis

Parameter | Pantoprazole Sodium Delayed-Release Tablets DAY 10 | Intravenous Pantoprazole Sodium* DAY 7 | Intravenous Placebo DAY 7
Mean maximum acid output | 6.49 n=30 | 6.62 n=23 | 29.19** n=7
Mean basal acid output | 0.80 n=30 | 0.53 n=23 | 4.14** n=7

* another intravenous pantoprazole sodium product
**p<0.0001 Significantly different from intravenous pantoprazole sodium.

To evaluate the effectiveness of intravenous pantoprazole sodium as an initial treatment to suppress gastric acid secretion, two studies were conducted.

Study 1 was a multicenter, double-blind, placebo-controlled, study of the pharmacodynamic effects of intravenous and oral pantoprazole sodium. Patients with GERD and a history of EE (n=78, 20 to 67 years; 39 females; 7 Black, 19 Hispanic, 52 White) were randomized to receive either 40 mg pantoprazole intravenously, 40 mg pantoprazole orally, or placebo once daily for 7 days. Following an overnight fast, test medication was administered and patients were given a light meal within 15 minutes. MAO and BAO were determined 24 hours following the last day of study medication. MAO was estimated from a 1 hour continuous collection of gastric contents following subcutaneous injection of 6 mcg/kg of pentagastrin to stimulate acid secretion. This study demonstrated that, after treatment for 7 days, patients treated with intravenous pantoprazole sodium had a significantly lower MAO and BAO than those treated with placebo (p<0.001), and results were comparable to those of patients treated with oral pantoprazole sodium (see Table 5).

Table 5: Antisecretory Effects (mEq/h) of Initial Treatment with 40 mg Intravenous Pantoprazole Sodium* and 40 mg Oral Pantoprazole in GERD Patients with a History of Erosive Esophagitis

Parameter | Intravenous Pantoprazole Sodium* DAY 7 | Pantoprazole Sodium Delayed-Release Tablets DAY 7 | Placebo DAY 7
Maximum acid output (mean ±SD) | 8.4 ± 5.9; n=25 | 6.3 ± 6.6; n=22 | 20.9 ± 14.5**; n=24
Basal acid output (mean±SD) | 0.4 ± 0.5; n=25 | 0.6 ± 0.8; n=22 | 2.8 ± 3**; n=23

* another intravenous pantoprazole sodium product
** p<0.0001 Significantly different from intravenous pantoprazole sodium

Study 2 was a single-center, double-blind, parallel-group study to compare the clinical effects of intravenous and oral pantoprazole sodium. Patients (n=45, median age 56 years, 21 males and 24 females) with acute endoscopically proven reflux esophagitis (Savary/Miller Stage II or III) with at least 1 of 3 symptoms typical for reflux esophagitis (acid eructation, heartburn, or pain on swallowing) were randomized to receive either 40 mg intravenous pantoprazole or 40 mg oral pantoprazole once daily for 5 days. After the initial 5 days, all patients were treated with 40 mg oral pantoprazole daily to complete a total of 8 weeks of treatment. Symptom relief was assessed by calculating the daily mean of the sums of the average scores for these 3 symptoms and the daily mean of the average score for each of the symptoms separately. There was no significant difference in symptom relief between intravenous and oral pantoprazole sodium therapy within the first 5 days. A repeat endoscopy after 8 weeks of treatment revealed that 20 out of 23 (87%) of the intravenous plus oral pantoprazole sodium patients and 19 out of 22 (86%) of the oral pantoprazole sodium patients had endoscopically proven healing of their esophageal lesions.

Data comparing intravenous pantoprazole sodium to other PPIs (oral or intravenous) or H2-receptor antagonists (oral or intravenous) are limited, and therefore, are inadequate to support any conclusions regarding comparative efficacy.

14.2 Pathological Hypersecretion Associated with Zollinger-Ellison Syndrome

Two studies measured the pharmacodynamic effects of 6 day treatment with intravenous pantoprazole sodium in patients with ZE Syndrome (with and without multiple endocrine neoplasia type I). In one of these studies, an initial treatment with intravenous pantoprazole sodium in 21 patients (29 to 75 years; 8 female; 4 Black, 1 Hispanic, 16 White) reduced acid output to the target level (less than or equal to 10 mEq/h) and significantly reduced H^+ concentration and the volume of gastric secretions; target levels were achieved within 45 minutes of drug administration.

In the other study of 14 patients (38 to 67 years; 5 female; 2 Black, 12 White) with ZE Syndrome, treatment was switched from an oral PPI to intravenous pantoprazole sodium. Intravenous pantoprazole sodium maintained or improved control of gastric acid secretion.

In both studies, total doses of 160 or 240 mg intravenous pantoprazole, administered in divided doses, maintained basal acid secretion below target levels in all patients. Target levels were 10 mEq/hour in patients without prior gastric surgery, and 5 mEq/h in all patients with prior gastric acid-reducing surgery. Once gastric acid secretion was controlled, there was no evidence of tolerance during this 7 day study. Basal acid secretion was maintained below target levels for at least 24 hours in all patients and through the end of treatment in these studies (3 to 7 days) in all but 1 patient who required a dose adjustment guided by acid output measurements until acid control was achieved. In both studies, doses were adjusted to the individual patient need, but gastric acid secretion was controlled in greater than 80% of patients by a starting regimen of 80 mg every 12 hours.

16 HOW SUPPLIED/STORAGE AND HANDLING

How Supplied

Pantoprazole Sodium for Injection is supplied in a single-dose vial as a white to off-white sterile lyophilized powder for reconstitution containing 40 mg of pantoprazole.

Pantoprazole Sodium for Injection is available as follows:

NDC Number | Strength | Package Size
55154-7477-5 | 40 mg pantoprazole | Overbagged with 5 single-dose vials per bag

WARNING: This Unit Dose package is not child resistant and is Intended for Institutional Use Only. Keep this and all drugs out of the reach of children.

Storage and Handling

Store at 20° to 25°C (68° to 77°F); excursions permitted to 15° to 30°C (59° to 86°F) [see USP Controlled Room Temperature].

Protect from light.

17 PATIENT COUNSELING INFORMATION

Adverse Reactions

Advise patients to report to their healthcare provider if they experience any signs or symptoms consistent with:

• Injection Site Reactions [see Warnings and Precautions (5.2)]

• Acute Tubulointerstitial Nephritis [see Warnings and Precautions (5.3)]

• Clostridium difficile-Associated Diarrhea [see Warnings and Precautions (5.4)]

• Bone Fracture [see Warnings and Precautions (5.5)]

• Severe Cutaneous Adverse Reactions [see Warnings and Precautions (5.6)]

• Cutaneous and Systemic Lupus Erythematosus [see Warnings and Precautions (5.7)]

• Hepatic Effects [see Warnings and Precautions (5.8)]

• Hypomagnesemia and Mineral Metabolism [see Warnings and Precautions (5.9)]

Drug Interactions

Advise patients to report to their healthcare provider before they start treatment with any of the following:

• Rilpivirine-containing products [see Contraindications (4)]

• High-dose methotrexate [see Warnings and Precautions (5.13)]

Pregnancy

Advise a pregnant woman of the potential risk to a fetus. Advise females of reproductive potential to inform their prescriber of a known or suspected pregnancy [see Use in Specific Populations (8.1)].

Manufactured by: HIKMA FARMACÊUTICA (PORTUGAL), S.A.
Estrada do Rio da Mό, 8, 8A e 8B – Fervença – 2705-906 Terrugem SNT, PORTUGAL

Distributed by:
Hikma Pharmaceuticals USA Inc.
Berkeley Heights, NJ 07922

Distributed By:

Cardinal Health

Dublin, OH 43017

L54670970924

PIN469-WES/8

Revised: July 2023

Package/Label Display Panel

NDC 55154-7477-5

PANTOPRAZOLE SODIUM

FOR INJECTION

Equivalent to pantoprazole

40 mg per vial

5 VIALS